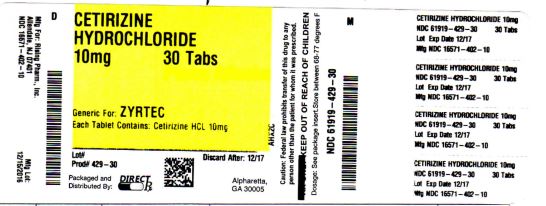 DRUG LABEL: CETIRIZINE HYDROCHLORIDE
NDC: 61919-429 | Form: TABLET
Manufacturer: DIRECT RX
Category: prescription | Type: HUMAN PRESCRIPTION DRUG LABEL
Date: 20230112

ACTIVE INGREDIENTS: CETIRIZINE HYDROCHLORIDE 10 mg/1 1
INACTIVE INGREDIENTS: MAGNESIUM STEARATE; STARCH, CORN; POLYETHYLENE GLYCOL, UNSPECIFIED; POVIDONE; TITANIUM DIOXIDE; HYPROMELLOSES; LACTOSE

CETIRIZINE HYDROCHLORIDE

Do Not Use if you have ever had an allergic reaction to this product or any of its ingredients or to an antihistamine containing hydroxyzine.

Active Ingredients (in each tablet) Purpose
Cetirizine HCl 10 mg..............................................................................................Antihistimine

Uses

Temporarily relieves these symptoms due to hay fever or other upper respiratory allergies

runny nose
sneezing
itchy, watery eyes
itching of the nose or throat

Ask a doctor before use if you have liver or kidney disease. Your doctor should determine if you need a different dose.

Ask a doctor or pharmacist before use if you are taking tranquilizers or sedatives.

WHEN USING

drowsines may occur
avoid alcoholic drinks
alcohol, sedatives, and tranquilizers may increase drowsiness
be careful when driving a motor vehicle or operating machinary.

Stop use and ask a doctor if an allergic reaction to this product occurs. Seek medical help right away.

if breast-feeding: not recommended
if pregnant: ask a health professional before use.

KEEP OUT OF REACH OF CHILDREN

In case of overdose, get medical help or contact Poison Control Center right away.

QUESTIONS

Adults and children 6
years and over
one 10 mg tablet once daily, do not take more than one 10 mg tablet in 24 hours. A 5 mg product may be appropriate for less sever symptoms.
Adults 65 years and over
Ask a doctor
Children under 6 years of age
Ask a doctor
Consumers with liver or kidney disease
Ask a doctor